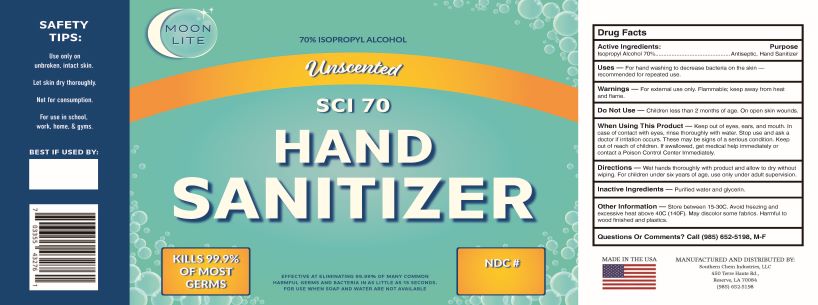 DRUG LABEL: SCI 70 Hand Sanitizer
NDC: 55549-018 | Form: LIQUID
Manufacturer: Southern Chem Industries LLC
Category: otc | Type: HUMAN OTC DRUG LABEL
Date: 20201016

ACTIVE INGREDIENTS: ISOPROPYL ALCOHOL 70 mL/100 mL
INACTIVE INGREDIENTS: GLYCERIN 1.45 mL/100 mL; WATER

IPA 70 Liquid No Fragrance

1. Isopropyl Alcohol (USP or Food Chemical Codex (FCC) grade) (70%, volume/volume (v/v)) in an aqueous solution denatured according to Alcohol and Tobacco Tax and Trade Bureau regulations in 27 CFR part 20.
2. Glycerol (1.45% v/v).
3. Sterile distilled water or boiled cold water.

.

Active Ingredient(s)

Isopropyl Alcohol 70% v/v. Purpose: Antiseptic

Purpose

Antiseptic, Hand Sanitizer

Use

For Hand-washing to decrease bacteria on skin - recommended for repeat use.

Warnings

For external use only. Flammable. Keep away from heat or flame

Do not use

- in children less than 2 months of age
- on open skin wounds

When using this product keep out of eyes, ears, and mouth. In case of contact with eyes, rinse eyes thoroughly with water.
Stop use and ask a doctor if irritation or rash occurs. These may be signs of a serious condition.
Keep out of reach of children. If swallowed, get medical help or contact a Poison Control Center immediately

Stop use and ask a doctor if irritation or rash occurs. These may be signs of a serious condition.

Keep out of reach of children. If swallowed, get medical help or contact a Poison Control Center right away.

Directions

- Wet hands thoroughly with product, and allow to dry without wiping. For Children under six, use only under adult supervision.

Other information

- Store between 15-30C (59-86F)
- Avoid freezing and excessive heat above 40C (104F)

Inactive ingredients

Purified water, and Glycerin